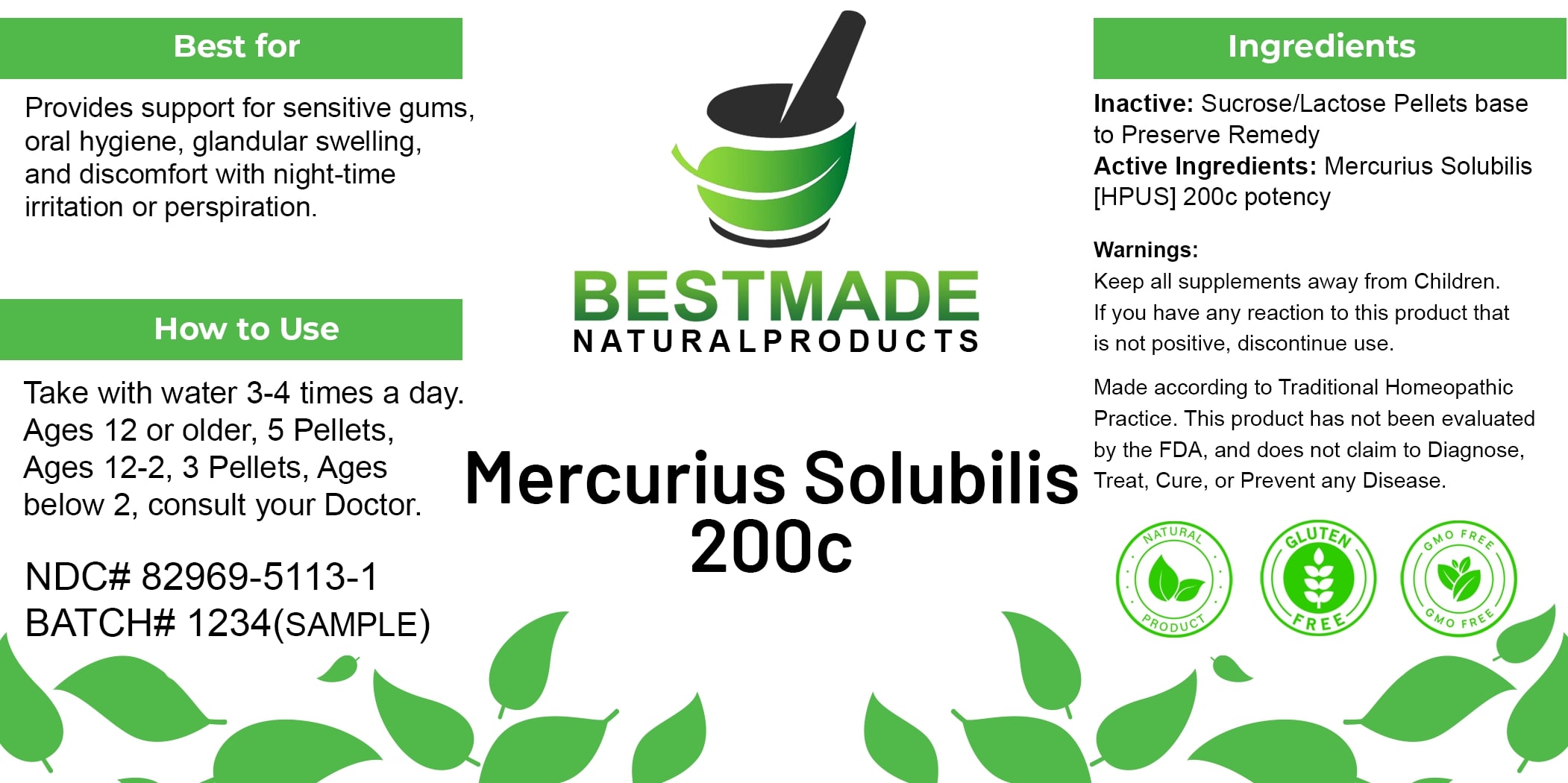 DRUG LABEL: Bestmade Natural Products Mercurius Solubilis
NDC: 82969-5113 | Form: TABLET, SOLUBLE
Manufacturer: Bestmade Natural Products
Category: homeopathic | Type: HUMAN OTC DRUG LABEL
Date: 20241219

ACTIVE INGREDIENTS: MERCURIUS SOLUBILIS 200 [hp_C]/200 [hp_C]
INACTIVE INGREDIENTS: SUCROSE 200 [hp_C]/200 [hp_C]; LACTOSE 200 [hp_C]/200 [hp_C]

Mercurius Solubilis 200C

DOSAGE AND ADMINISTRATION

Take with water 3-4 times a day

Ages 12 or older, 5 Pellets, Ages 12-2, 3 Pellets, Ages below 2, consult your Doctor.

INDICATIONS AND USAGE

Best for

Provides support for sensitive gums oral hygiene, glandular swelling, and discomfort with night-time irritation or perspiration.

Inactive: Sucrose/Lactose Pellets base to Preserve Remedy

Active Ingredients: Mercurius Solubilis [HPUS] 200c potency

Warnings:

Keep all supplements away from Children.

If you have any reaction to this product that is not positive, discontinue use.

Made according to Traditional Homeopathic Practice. This product has not been evaluated by the FDA, and does not claim to Diagnose, Treat, Cure, or Prevent any Disease.

PURPOSE

Best for

Provides support for sensitive gums oral hygiene, glandular swelling, and discomfort with night-time irritation or perspiration.

Warnings:

Keep all supplements away from Children.

If you have any reaction to this product that is not positive, discontinue use.

Made according to Traditional Homeopathic Practice. This product has not been evaluated by the FDA, and does not claim to Diagnose, Treat, Cure, or Prevent any Disease.

Entire package label